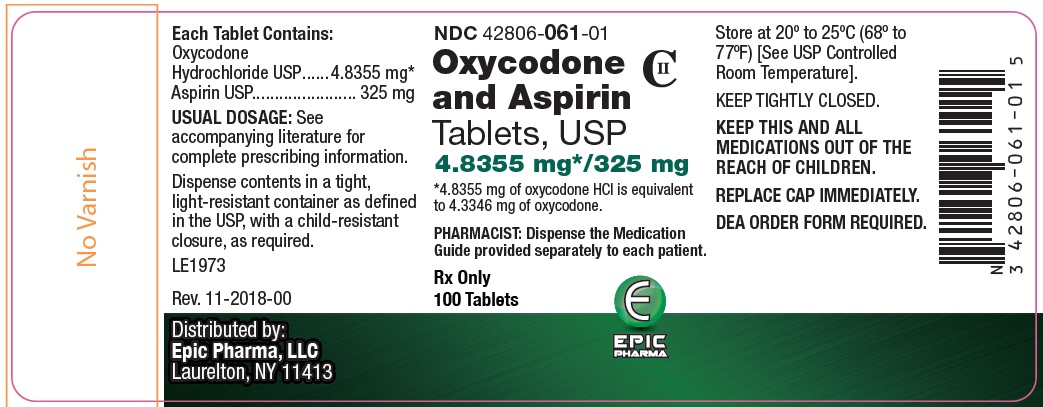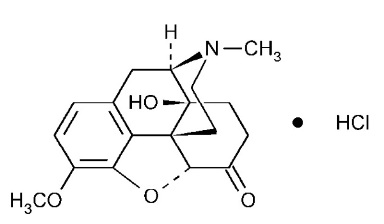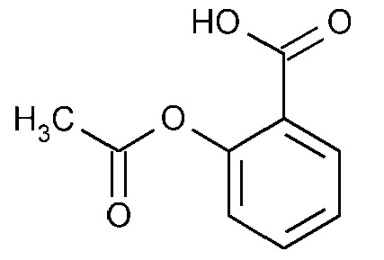 DRUG LABEL: Oxycodone and Aspirin
NDC: 42806-061 | Form: TABLET
Manufacturer: Epic Pharma, LLC
Category: prescription | Type: HUMAN PRESCRIPTION DRUG LABEL
Date: 20251217
DEA Schedule: CII

ACTIVE INGREDIENTS: OXYCODONE HYDROCHLORIDE 4.8355 mg/1 1; ASPIRIN 325 mg/1 1
INACTIVE INGREDIENTS: MICROCRYSTALLINE CELLULOSE; STARCH, CORN; ZINC STEARATE

Oxycodone and Aspirin Tablets Cll

WARNING: SERIOUS AND LIFE-THREATENING RISKS FROM USE OF OXYCODONE AND ASPIRIN TABLETS

Addiction, Abuse, and Misuse

Because the use of oxycodone and aspirin tablets exposes patients and other users to the risks of opioid addiction, abuse, and misuse, which can lead to overdose and death, assess each patient’s risk prior to prescribing and reassess all patients regularly for the development of these behaviors and conditions (see WARNINGS).

Life-Threatening Respiratory Depression

Serious, life-threatening, or fatal respiratory depression may occur with use of oxycodone and aspirin tablets, especially during initiation or following a dosage increase. To reduce the risk of respiratory depression, proper dosing and titration of oxycodone and aspirin tablets are essential (see WARNINGS).

Accidental Ingestion

Accidental ingestion of even one dose of oxycodone and aspirin tablets, especially by children, can result in a fatal overdose of oxycodone (see WARNINGS).

Risks From Concomitant Use With Benzodiazepines Or Other CNS Depressants

Concomitant use of opioids with benzodiazepines or central nervous system (CNS) depressants, including alcohol, may result in profound sedation, respiratory depression, coma, and death. Reserve concomitant prescribing of oxycodone and aspirin tablets and benzodiazepines or other CNS depressants for use in patients for whom alternative treatment options are inadequate [see WARNINGS].

Neonatal Opioid Withdrawal Syndrome (NOWS)

If opioid use is required for an extended period of time in a pregnant woman, advise the patient of the risk of NOWS, which may be life-threatening if not recognized and treated. Ensure that management by neonatology experts will be available at delivery [see WARNINGS].

Opioid Analgesic Risk Evaluation and Mitigation Strategy (REMS):

Healthcare providers are strongly encouraged to complete a REMS-compliant education program and to counsel patients and caregivers on serious risks, safe use, and the importance of reading the Medication Guide with each prescription [see WARNINGS].

Cytochrome P450 3A4 Interaction

The concomitant use of oxycodone and aspirin tablets with all cytochrome P450 3A4 inhibitors may result in an increase in oxycodone plasma concentrations, which could increase or prolong adverse reactions and may cause potentially fatal respiratory depression. In addition, discontinuation of a concomitantly used cytochrome P450 3A4 inducer may result in an increase in oxycodone plasma concentration. Regularly evaluate patients receiving oxycodone and aspirin tablets and any CYP3A4 inhibitor or inducer frequently (see CLINICAL PHARMACOLOGY, WARNINGS, PRECAUTIONS; Drug Interactions).

DESCRIPTION

Oxycodone and Aspirin Tablets are an immediate-release opioid agonist intended for oral administration only.

Each Oxycodone and Aspirin Tablet contains:

Oxycodone Hydrochloride, USP 4.8355 mg*

Aspirin, USP 325 mg

*4.8355 mg oxycodone HCl is equivalent to 4.3346 mg of oxycodone as the free base.

Oxycodone and Aspirin Tablets USP also contain the following inactive ingredients: microcrystalline cellulose, starch and zinc stearate.

C18N21NO4 •HCl MW 351.82

The oxycodone hydrochloride component is Morphinan-6-one, 4,5-epoxy-14-hydroxy-3-methoxy-17-methyl-, hydrochloride, (5α)-, a white to off-white, hygroscopic crystals or powder, odorless, soluble in water; slightly soluble in alcohol and is represented by the following structural formula:

C9H8O4 MW 180.16

CLINICAL PHARMACOLOGY

Mechanism of Action

Oxycodone is a full opioid agonist and is relatively selective for the mu-opioid receptor, although it can bind to other opioid receptors at higher doses. The principal therapeutic action of oxycodone is analgesia. Like all full opioid agonists, there is no ceiling effect for analgesia with oxycodone. Clinically, dosage is titrated to provide adequate analgesia and may be limited by adverse reactions, including respiratory and CNS depression.

The precise mechanism of the analgesic action of oxycodone is unknown. However, specific CNS opioid receptors for endogenous compounds with opioid-like activity have been identified throughout the brain and spinal cord and are thought to play a role in the analgesic effects of this drug.

Aspirin (acetylsalicylic acid) works by inhibiting the body’s production of prostaglandins, including prostaglandins involved in inflammation. Prostaglandins cause pain sensations by stimulating muscle contractions and dilating blood vessels throughout the body. In the CNS, aspirin works on the hypothalamus heat-regulating center to reduce fever, however, other mechanisms may be involved.

Pharmacodynamics

Effects on the Central Nervous System

Oxycodone produces respiratory depression by direct action on brain stem respiratory centers. The respiratory depression involves a reduction in the responsiveness of the brain stem respiratory centers to increases in both carbon dioxide tension and electrical stimulation.

Oxycodone causes miosis, even in total darkness. Pinpoint pupils are a sign of opioid overdose but are not pathognomonic (e.g., pontine lesions of hemorrhagic or ischemic origins may produce similar findings). Marked mydriasis rather than miosis may be seen due to hypoxia in overdose situations.

Effects on the Gastrointestinal Tract and Other Smooth Muscle

Oxycodone causes a reduction in motility associated with an increase in smooth muscle tone in the antrum of the stomach and duodenum. Digestion of food in the small intestine is delayed and propulsive contractions are decreased. Propulsive peristaltic waves in the colon are decreased, while tone may be increased to the point of spasm resulting in constipation. Other opioid-induced effects may include a reduction in biliary and pancreatic secretions, spasm of sphincter of Oddi, and transient elevations in serum amylase.

Aspirin can produce gastrointestinal injury (lesions, ulcers) through a mechanism that is not yet completely understood, but may involve a reduction in eicosanoid synthesis by the gastric mucosa. Decreased production of prostaglandins may compromise the defenses of the gastric mucosa and the activity of substances involved in tissue repair and ulcer healing.

Effects on the Cardiovascular System

Oxycodone produces peripheral vasodilation which may result in orthostatic hypotension or syncope. Manifestations of histamine release and/or peripheral vasodilation may include pruritus, flushing, red eyes and sweating and/or orthostatic hypotension.

Use caution in hypovolemic patients, such as those suffering acute myocardial infarction, because oxycodone may cause or further aggravate their hypotension. Caution must also be used in patients with cor pulmonale who have received therapeutic doses of opioids.

Effects on the Endocrine System

Opioids inhibit the secretion of adrenocorticotropic hormone (ACTH), cortisol, and luteinizing hormone (LH) in humans (see ADVERSE REACTIONS). They also stimulate prolactin, growth hormone (GH) secretion, and pancreatic secretion of insulin and glucagon.

Use of opioids for an extended period of time may influence the hypothalamic-pituitary-gonadal axis, leading to androgen deficiency that may manifest as low libido, impotence, erectile dysfunction, amenorrhea, or infertility. The causal role of opioids in the clinical syndrome of hypogonadism is unknown because the various medical, physical, lifestyle, and psychological stressors that may influence gonadal hormone levels have not been adequately controlled for in studies conducted to date (see ADVERSE REACTIONS).

Effects on the Immune System

Opioids have been shown to have a variety of effects on components of the immune system in in vitro and animal models. The clinical significance of these findings is unknown. Overall, the effects of opioids appear to be modestly immunosuppressive.

Concentration–Efficacy Relationships

The minimum effective analgesic concentration will vary widely among patients, especially among patients who have been previously treated with opioid agonists. The minimum effective analgesic concentration of oxycodone for any individual patient may increase over time due to an increase in pain, the development of a new pain syndrome and/or the development of analgesic tolerance (see DOSAGE AND ADMINISTRATION).

Concentration–Adverse Reaction Relationships

There is a relationship between increasing oxycodone plasma concentration and increasing frequency of dose-related opioid adverse reactions such as nausea, vomiting, CNS effects, and respiratory depression. In opioid-tolerant patients, the situation may be altered by the development of tolerance to opioid-related adverse reactions (see DOSAGE AND ADMINISTRATION).

The dose of oxycodone and aspirin tablets must be individualized because the effective analgesic dose for some patients will be too high to be tolerated by other patients (see DOSAGE AND ADMINISTRATION).

Platelet Aggregation

Aspirin affects platelet aggregation by irreversibly inhibiting prostaglandin cyclo-oxygenase. This effect lasts for the life of the platelet and prevents the formation of the platelet aggregating factor thromboxane A2. Nonacetylated salicylates do not inhibit this enzyme and have no effect on platelet aggregation. At somewhat higher doses, aspirin reversibly inhibits the formation of prostaglandin 12 (prostacyclin), which is an arterial vasodilator and inhibits platelet aggregation.

Pharmacokinetics

Absorption

The mean absolute oral bioavailability of oxycodone in cancer patients was reported to be about 87%. This high oral bioavailability is due to low pre-systemic elimination and/or first-pass metabolism.

Distribution

The volume of distribution after intravenous administration is 211.9 ±186.6 L. Oxycodone has been shown to be 45% bound to human plasma proteins in vitro. Oxycodone has been found in breast milk (see PRECAUTIONS).

Aspirin is hydrolyzed primarily to salicylic acid in the gut wall and during first-pass metabolism through the liver. Salicylic acid is absorbed rapidly from the stomach, but most of the absorption occurs in the proximal small intestine. Following absorption, salicylate is distributed to most body tissues and fluids, including fetal tissues, breast milk, and the CNS. High concentrations are found in the liver and kidneys. Salicylate is variably bound to serum proteins, particularly albumin.

Elimination

Metabolism

Oxycodone is extensively metabolized by multiple metabolic pathways to produce noroxycodone, oxymorphone and noroxymorphone, which are subsequently glucuronidated. Noroxycodone and noroxymorphone are the major circulating metabolites. CYP3A mediated N-demethylation to noroxycodone is the primary metabolic pathway of oxycodone with a lower contribution from CYP2D6 mediated O-demethylation to oxymorphone. Therefore, the formation of these and related metabolites can, in theory, be affected by other drugs (see Drug-Drug Interactions).

Noroxycodone exhibits very weak anti-nociceptive potency compared to oxycodone, however, it undergoes further oxidation to produce noroxymorphone, which is active at opioid receptors. Although noroxymorphone is an active metabolite and present at relatively high concentrations in circulation, it does not appear to cross the blood-brain barrier to a significant extent. Oxymorphone, is present in the plasma only at low concentrations and undergoes further metabolism to form its glucuronide and noroxymorphone. Oxymorphone has been shown to be active and possessing analgesic activity but its contribution to analgesia following oxycodone administration is thought to be clinically insignificant, based on the amount formed. Other metabolites (α-and ß-oxycodol, noroxycodol and oxymorphol) may be present at very low concentrations and demonstrate limited penetration into the brain as compared to oxycodone. The enzymes responsible for keto-reduction and glucuronidation pathways in oxycodone metabolism have not been established.

The biotransformation of aspirin occurs primarily in the liver by the microsomal enzyme system. With a plasma half-life of approximately 15 minutes, aspirin is rapidly hydrolyzed to salicylate. At low doses, salicylate elimination follows first-order kinetics. The plasma half-life of salicylate is approximately 2 to 3 hours.

Excretion

Free and conjugated noroxycodone, free and conjugated oxycodone, and oxymorphone are excreted in human urine following a single oral dose of oxycodone. Approximately 8% to 14% of the dose is excreted as free oxycodone over 24 hours after administration.

Approximately 10% of aspirin is excreted as unchanged salicylate in the urine. The major metabolites excreted in the urine are salicyluric acid (75%), salicyl phenolic glucuronide (10%), salicyl acyl glucuronide (5%), and gentisic and gentisuric acid (less than 1%) each. Eighty to 100% of a single dose is excreted in the urine within 24 to 72 hours.

Drug -Drug Interactions (see PRECAUTIONS)

Inhibitors of CYP3A4

Since the CYP3A4 isoenzyme plays a major role in the metabolism of oxycodone and aspirin tablets, drugs that inhibit CYP3A4 activity, such as macrolide antibiotics (e.g., erythromycin), azole-antifungal agents (e.g., ketoconazole), and protease inhibitors (e.g., ritonavir), may cause decreased clearance of oxycodone, which could lead to an increase in oxycodone plasma concentrations. A published study showed that the co-administration of the antifungal drug, voriconazole, increased oxycodone AUC and Cmax by 3.6 and 1.7 fold, respectively. The expected clinical results would be increased or prolonged opioid effects.

Inducers of CYP450

CYP450 inducers, such as rifampin, carbamazepine, and phenytoin, may induce the metabolism of oxycodone, may cause increased clearance of the drug which could lead to a decrease in oxycodone plasma concentrations. A published study showed that the co-administration of rifampin, a drug metabolizing enzyme inducer, decreased oxycodone (oral) AUC and Cmax by 86% and 63% respectively. The expected clinical results would be lack of efficacy or, possibly, development of abstinence syndrome in a patient who had developed physical dependence to oxycodone. Induction of CYP3A4 may be of greatest importance given oxycodone’s metabolic pathways.

INDICATIONS AND USAGE

Oxycodone and aspirin tablets are indicated for the management of pain severe enough to require an opioid analgesic and for which alternative treatments are inadequate.

Limitations of Use

Because of the risks of addiction, abuse, and misuse, with opioids, which can occur at any dosage or duration (see WARNINGS), reserve oxycodone and aspirin tablets for use in patients for whom alternative treatment options (e.g., non-opioid analgesics)

- Have not been tolerated, or are not expected to be tolerated,
- Have not provided adequate analgesia, or are not expected to provide adequate analgesia

Oxycodone and Aspirin tablets should not be used for an extended period of time unless the pain remains severe enough to require an opioid analgesic and for which alternative treatment options continue to be inadequate.

CONTRAINDICATIONS

Oxycodone and aspirin tablets are contraindicated in patients with:

- Significant respiratory depression (see WARNINGS)
- Acute or severe bronchial asthma in an unmonitored setting or in the absence of resuscitative equipment (see WARNINGS)
- Known or suspected gastrointestinal obstruction, including paralytic ileus (see WARNINGS)
- Hypersensitivity to oxycodone or aspirin, (e.g. angioedema) (see WARNINGS)
- Patients with hemophilia.
- Aspirin should not be used in children or teenagers for viral infections, with or without fever, because of the risk of Reye syndrome (see WARNINGS)

WARNINGS

Addiction, Abuse, and Misuse

Oxycodone and aspirin tablets contain Oxycodone, a Schedule II controlled substance. As an opioid, oxycodone and aspirin tablets exposes users to the risks of addiction, abuse, and misuse (see DRUG ABUSE AND DEPENDENCE).

Although the risk of addiction in any individual is unknown, it can occur in patients appropriately prescribed oxycodone and aspirin tablets. Addiction can occur at recommended dosages and if the drug is misused or abused.

Assess each patient’s risk for opioid addiction, abuse, or misuse prior to prescribing oxycodone and aspirin tablets, and reassess all patients receiving oxycodone and aspirin tablets for the development of these behaviors and conditions. Risks are increased in patients with a personal or family history of substance abuse (including drug or alcohol abuse or addiction) or mental illness (e.g., major depression). The potential for these risks should not, however, prevent the proper management of pain in any given patient. Patients at increased risk may be prescribed opioids such as oxycodone and aspirin tablets but use in such patients necessitates intensive counseling about the risks and proper use of oxycodone and aspirin tablets along with frequent reevaluation for signs of addiction, abuse, and misuse. Consider prescribing naloxone for the emergency treatment of opioid overdose [see WARNINGS, DOSAGE AND ADMINISTRATION].

Opioids are sought by nonmedical use and are subject to diversion from legitimate prescribed use. Consider these risks when prescribing or dispensing oxycodone and aspirin tablets. Strategies to reduce these risks include prescribing the drug in the smallest appropriate quantity and advising the patient on careful storage of the drug during the course of treatment and proper disposal of unused drug (see PRECAUTIONS; Information for Patients/Caregivers). Contact local state professional licensing board or state-controlled substances authority for information on how to prevent and detect abuse or diversion of this product.

Life-Threatening Respiratory Depression

Serious, life-threatening, or fatal respiratory depression has been reported with the use of opioids, even when used as recommended. Respiratory depression, if not immediately recognized and treated, may lead to respiratory arrest and death. Management of respiratory depression may include close observation, supportive measures, and use of opioid antagonists, depending on the patient’s clinical status (see OVERDOSAGE). Carbon dioxide (CO2) retention from opioid-induced respiratory depression can exacerbate the sedating effects of opioids.

While serious, life-threatening, or fatal respiratory depression can occur at any time during the use of oxycodone and aspirin tablets, the risk is greatest during the initiation of therapy or following a dosage increase.

To reduce the risk of respiratory depression, proper dosing and titration of oxycodone and aspirin tablets are essential (see DOSAGE AND ADMINISTRATION). Overestimating the oxycodone and aspirin tablets when converting patients from another opioid product can result in a fatal overdose with the first dose.

Accidental ingestion of even one dose of oxycodone and aspirin tablets, especially by children can result in respiratory depression and death due to an overdose of oxycodone. Educate patients and caregivers on how to recognize respiratory depression and emphasize the importance of calling 911 or getting emergency medical help right away in the event of a known or suspected overdose [see PRECAUTIONS; Information for Patients/Caregivers].

Opioids can cause sleep-related breathing disorders including central sleep apnea (CSA) and sleep-related hypoxemia. Opioid use increases the risk of CSA in a dose-dependent fashion. In patients who present with CSA, consider decreasing the opioid dosage using best practices for opioid taper (see DOSAGE AND ADMINISTRATION).

Patients Access to Naloxone for the Emergency Treatment of Opioid Overdose

Discuss the availability of naloxone for the emergency treatment of opioid overdose with the patient and caregiver and assess the potential need for access to naloxone, both when initiating and renewing treatment with oxycodone and aspirin tablets. Inform patients and caregivers about the various ways to obtain naloxone as permitted by individual state naloxone dispensing and prescribing requirements or guidelines (e.g., by prescription, directly from a pharmacist, or as part of a community-based program). Educate patients and caregivers on how to recognize respiratory depression and emphasize the importance of calling 911 or getting emergency medical help, even if naloxone is administered [see PRECAUTIONS; Information for Patients/Caregivers].

Consider prescribing naloxone, based on the patient’s risk factors for overdose, such as concomitant use of other CNS depressants, a history of opioid use disorder, or prior opioid overdose. The presence of risk factors for overdose should not prevent the proper management of pain in any given patient. Also consider prescribing naloxone if the patient has household members (including children) or other close contacts at risk for accidental ingestion or overdose. If naloxone is prescribed, educate patients and caregivers on how to treat with naloxone [see WARNINGS, PRECAUTIONS; Information for Patients/Caregivers, OVERDOSAGE].

Risks from Concomitant Use with Benzodiazepines or Other CNS Depressants

Profound sedation, respiratory depression, coma, and death may result from the concomitant use of oxycodone and aspirin tablets with benzodiazepines and/or other CNS depressants, including alcohol (e.g., nonbenzodiazepine sedatives/hypnotics, anxiolytics, tranquilizers, muscle relaxants, general anesthetics, antipsychotics, other opioids). Because of these risks, reserve concomitant prescribing of these drugs for use in patients for whom alternative treatment options are inadequate.

Observational studies have demonstrated that concomitant use of opioid analgesics and benzodiazepines increases the risk of drug-related mortality compared to use of opioid analgesics alone. Because of similar pharmacological properties, it is reasonable to expect similar risk with the concomitant use of other CNS depressant drugs with opioid analgesics [see PRECAUTIONS; Drug Interactions].

If the decision is made to prescribe a benzodiazepine or other CNS depressant concomitantly with an opioid analgesic, prescribe the lowest effective dosages and minimum durations of concomitant use. In patients already receiving an opioid analgesic, prescribe a lower initial dose of the benzodiazepine or other CNS depressant than indicated in the absence of an opioid, and titrate based on clinical response. If an opioid analgesic is initiated in a patient already taking a benzodiazepine or other CNS depressant, prescribe a lower initial dose of the opioid analgesic, and titrate based on clinical response. Inform patients and caregivers of this potential interaction and educate them on the signs and symptoms of respiratory depression (including sedation).

If concomitant use is warranted, consider prescribing naloxone for the emergency treatment of opioid overdose [see WARNINGS, DOSAGE AND ADMINISTRATION].

Advise both patient and caregivers about the risks of respiratory depression and sedation when oxycodone and aspirin tablets is used with benzodiazepines or other CNS depressants (including alcohol and illicit drugs). Advise patients not to drive or operate heavy machinery until the effects of concomitant use of the benzodiazepine or other CNS depressant have been determined. Screen patients for risk of substance use disorders, including opioid abuse and misuse; and warn them of the risk for overdose and death associated with the use of additional CNS depressants including alcohol and illicit drugs [see PRECAUTIONS; Drug Interactions].

Neonatal Opioid Withdrawal Syndrome

Use of oxycodone and aspirin tablets for an extended period of time during pregnancy can result in withdrawal in the neonate. Neonatal opioid withdrawal syndrome, unlike opioid withdrawal syndrome in adults, may be life-threatening if not recognized and treated, and requires management according to protocols developed by neonatology experts. Observe newborns for signs of neonatal opioid withdrawal syndrome and manage accordingly. Advise pregnant women using opioids for an extended period of time of the risk of neonatal opioid withdrawal syndrome and ensure that appropriate treatment will be available (see PRECAUTIONS; Information for Patients/Caregivers, Pregnancy).

Risk Evaluation and Mitigation Strategy (REMS)

To ensure that the benefits of opioid analgesics outweigh the risks of addiction, abuse, and misuse, the Food and Drug Administration (FDA) has required a Risk Evaluation and Mitigation Strategy (REMS) for these products. Under the requirements of the REMS, drug companies with approved opioid analgesic products must make REMS-compliant education programs available to healthcare providers. Healthcare providers are strongly encouraged to do all of the following:

- Complete a REMS-compliant education program offered by an accredited provider of continuing education (CE) or another education program that includes all the elements of the FDA Education Blueprint for Health Care Providers Involved in the Management or Support of Patients with Pain.
- Discuss the safe use, serious risks, and proper storage and disposal of opioid analgesics with patients and/or their caregivers every time these medicines are prescribed. The Patient Counseling Guide (PCG) can be obtained at this link: www.fda.gov/OpioidAnalgesicREMSPCG.
- Emphasize to patients and their caregivers the importance of reading the Mediation Guide that they will receive from their pharmacist every time an opioid analgesic is dispended to them,
- Consider using other tools to improve patient, household, and community safety, such as patient-prescriber agreements that reinforce patient-prescriber responsibilities.
To obtain further information on the opioid analgesic REMS and for a list of accredited REMS and for a list of accredited REMS CME/CE, call 1-800-503-0784, or log on to www.opioidanalgesicrems.com. The FDA Blueprint can be found at www.fda.gov/OpioidAnalgesicREMSBlueprint.

Risks of Concomitant Use or Discontinuation of Cytochrome P450 3A4 Inhibitors and Inducers

Concomitant use of oxycodone and aspirin tablets with a CYP3A4 inhibitor, such as macrolide antibiotics (e.g., erythromycin), azole-antifungal agents (e.g., ketoconazole), and protease inhibitors (e.g., ritonavir), may increase plasma concentrations of oxycodone and prolong opioid adverse reactions, which may cause potentially fatal respiratory depression (see WARNINGS), particularly when an inhibitor is added after a stable dose of oxycodone and aspirin tablets is achieved. Similarly, discontinuation of a CYP3A4 inducer, such as rifampin, carbamazepine, and phenytoin, in oxycodone and aspirin tablets -treated patients may increase oxycodone and aspirin tablets plasma concentrations and prolong opioid adverse reactions. When using oxycodone and aspirin tablets with CYP3A4 inhibitors or discontinuing CYP3A4 inducers in oxycodone and aspirin tablets -treated patients, evaluate patients at frequent intervals and consider dosage reduction of oxycodone and aspirin tablets until stable drug effects are achieved (see PRECAUTIONS; Drug Interactions).

Concomitant use of oxycodone and aspirin tablets with CYP3A4 inducers or discontinuation of a CYP3A4 inhibitor could decrease oxycodone plasma concentrations, decrease opioid efficacy or, possibly, lead to a withdrawal syndrome in a patient who had developed physical dependence to oxycodone. When using oxycodone and aspirin tablets with CYP3A4 inducers or discontinuing CYP3A4 inhibitors, evaluate patients at frequent intervals and consider increasing the opioid dosage if needed to maintain adequate analgesia or if symptoms of opioid withdrawal occur (see PRECAUTIONS; Drug Interactions).

Opioid-Induced Hyperalgesia and Allodynia

Opioid-Induced Hyperalgesia (OIH) occurs when an opioid analgesic paradoxically causes an increase in pain, or an increase in sensitivity to pain. This condition differs from tolerance, which is the need for increasing doses of opioids to maintain a defined effect [see DRUG ABUSE AND DEPENDENCE]. Symptoms of OIH include (but may not be limited to) increased levels of pain upon opioid dosage increase, decreased levels of pain upon opioid dosage decrease, or pain from ordinarily non-painful stimuli (allodynia). These symptoms may suggest OIH only if there is no evidence of underlying disease progression, opioid tolerance, opioid withdrawal, or addictive behavior.

Cases of OIH have been reported, both with short-term and longer-term use of opioid analgesics. Through the mechanism of OIH is not fully understood, multiple biochemical pathways have been implicated. Medical literature suggests a strong biologic plausibility between opioid analgesics and OIH and allodynia. If a patient is suspected to be experiencing OIH, carefully consider appropriately decreasing the dose of the current opioid analgesic or opioid rotation (safely switching the patient to a different opioid moiety) [see WARNINGS, DOSAGE AND ADMINISTRATION].

Life-Threatening Respiratory Depression in Patients with Chronic Pulmonary Disease or in Elderly, Cachectic, or Debilitated Patients

The use of oxycodone and aspirin tablets in patients with acute or severe bronchial asthma in an unmonitored setting or in the absence of resuscitative equipment is contraindicated.

Patients with Chronic Pulmonary Disease: Oxycodone and aspirin tablets -treated patients with significant chronic obstructive pulmonary disease or cor pulmonale, and those with a substantially decreased respiratory reserve, hypoxia, hypercapnia, or pre-existing respiratory depression are at increased risk of decreased respiratory drive including apnea, even at recommended dosages of oxycodone and aspirin tablets (see WARNINGS).

Elderly, Cachectic, or Debilitated Patients: Life-threatening respiratory depression is more likely to occur in elderly, cachectic, or debilitated patients because they may have altered pharmacokinetics or altered clearance compared to younger, healthier patients (see WARNINGS).

Regularly evaluate patients, particularly when initiating and titrating oxycodone and aspirin tablets and when oxycodone and aspirin tablets is given concomitantly with other drugs that depress respiration (see WARNINGS). Alternatively, consider the use of non-opioid analgesics in these patients.

Adrenal Insufficiency

Cases of adrenal insufficiency have been reported with opioid use, more often following greater than 1 month of use. Presentation of adrenal insufficiency may include non-specific symptoms and signs including nausea, vomiting, anorexia, fatigue, weakness, dizziness, and low blood pressure. If adrenal insufficiency is suspected, confirm the diagnosis with diagnostic testing as soon as possible. If adrenal insufficiency is diagnosed, treat with physiologic replacement doses of corticosteroids. Wean the patient off of the opioid to allow adrenal function to recover and continue corticosteroid treatment until adrenal function recovers. Other opioids may be tried as some cases reported use of a different opioid without recurrence of adrenal insufficiency. The information available does not identify any particular opioids as being more likely to be associated with adrenal insufficiency.

Severe Hypotension

Oxycodone and aspirin tablets may cause severe hypotension including orthostatic hypotension and syncope in ambulatory patients. There is increased risk in patients whose ability to maintain blood pressure has already been compromised by a reduced blood volume or concurrent administration of certain CNS depressant drugs (e.g. phenothiazines or general anesthetics). Regularly evaluate these patients for signs of hypotension after initiating or titrating the dosage of oxycodone and aspirin tablets. In patients with circulatory shock, oxycodone and aspirin tablets may cause vasodilation that can further reduce cardiac output and blood pressure. Avoid the use of oxycodone and aspirin tablets in patients with circulatory shock.

Risks of Use in Patients with Increased Intracranial Pressure, Brain Tumors, Head Injury, or Impaired Consciousness

In patients who may be susceptible to the intracranial effects of CO2 retention (e.g., those with evidence of increased intracranial pressure or brain tumors), oxycodone and aspirin tablets may reduce respiratory drive, and the resultant CO2 retention can further increase intracranial pressure. Monitor such patients for signs of sedation and respiratory depression, particularly when initiating therapy with oxycodone and aspirin tablets.

Opioids may also obscure the clinical course in a patient with a head injury. Avoid the use of oxycodone and aspirin tablets in patients with impaired consciousness or coma.

Risks of Use in Patients with Gastrointestinal Conditions

Oxycodone and aspirin tablets are contraindicated in patients with known or suspected gastrointestinal obstruction, including paralytic ileus.

The oxycodone in oxycodone and aspirin tablets may cause spasm of the sphincter of Oddi. Opioids may cause increases in serum amylase. Regularly evaluate patients with biliary tract disease, including acute pancreatitis for worsening symptoms.

Increased Risk of Seizures in Patients with Seizure Disorders

The oxycodone in oxycodone and aspirin tablets may increase the frequency of seizures in patients with seizure disorders, and may increase the risk of seizures occurring in other clinical settings associated with seizures. Regularly evaluate patients with a history of seizure disorders for worsened seizure control during oxycodone and aspirin tablets therapy.

Withdrawal

Do not abruptly discontinue oxycodone and aspirin tablets in a patient physically dependent on opioids. When discontinuing oxycodone and aspirin tablets, in a physically dependent patient, gradually taper the dosage. Rapid tapering of oxycodone and aspirin in a patient physically dependent on opioids may lead to a withdrawal syndrome and return of pain (see DOSAGE AND ADMINISTRATION, DRUG ABUSE AND DEPENDENCE).

Additionally, avoid the use of mixed agonist/antagonist (i.e., pentazocine, nalbuphine, and butorphanol) or partial agonist (buprenorphine) analgesics in patients who have received or are receiving a course of therapy with a full opioid agonist analgesic, including oxycodone and aspirin tablets. In these patients, mixed agonist/antagonist and partial agonist analgesics may reduce the analgesic effect and/or may precipitate withdrawal symptoms. (see PRECAUTIONS; Drug Interactions).

Fetal Toxicity

Premature Closure of Fetal Ductus Arteriosus

Avoid use of NSAIDs, including oxycodone and aspirin tablets, in pregnant women at about 30 weeks gestation and later. NSAIDs including oxycodone and aspirin tablets, increase the risk of premature closure of the fetal ductus arteriosus at approximately this gestational age.

Oligohydramnios/Neonatal Renal Impairment

Use of NSAIDs, including oxycodone and aspirin tablets, at about 20 weeks gestation or later in pregnancy may cause fetal renal dysfunction leading to oligohydramnios and, in some cases, neonatal renal impairment. These adverse outcomes are seen, on average, after days to weeks of treatment, although oligohydramnios has been infrequently reported as soon as 48 hours after NSAID initiation.

Oligohydramnios is often, but not always, reversible with treatment discontinuation. Complications of prolonged oligohydramnios may, for example, include limb contractures and delayed lung maturation. In some postmarketing cases of impaired neonatal renal function, invasive procedures such as exchange transfusion or dialysis were required.

If NSAID treatment is necessary between about 20 weeks and 30 weeks gestation, limit oxycodone and aspirin tablets use to the lowest effective dose and shortest duration possible. Consider ultrasound monitoring of amniotic fluid if oxycodone and aspirin tablets treatment extends beyond 48 hours. Discontinue oxycodone and aspirin tablets if oligohydramnios occurs and follow up according to clinical practice [see PRECAUTIONS; Pregnancy].

Risks of Driving and Operating Machinery

Oxycodone and aspirin tablets may impair the mental or physical abilities needed to perform potentially hazardous activities such as driving a car or operating machinery. Warn patients not to drive or operate dangerous machinery unless they are tolerant to the effects of oxycodone and aspirin tablets and know how they will react to the medication (see PRECAUTIONS: Information for Patients/Caregivers).

Hypersensitivity to Oxycodone or Aspirin, (e.g. angioedema)

Oxycodone and aspirin tablets are contraindicated in patients with known hypersensitivity to oxycodone or aspirin, and in any situation where opioids or aspirin are contraindicated.

Reye Syndrome

Aspirin should not be used in children or teenagers for viral infections, with or without fever, because of the risk of Reye syndrome with concomitant use of aspirin in certain viral illnesses

Serious Skin Reactions

NSAIDs, including aspirin, a component of oxycodone and aspirin tablets, can cause serious skin adverse reactions such as exfoliative dermatitis, Stevens-Johnson Syndrome (SJS), and toxic epidermal necrolysis (TEN), which can be fatal. NSAIDs can also cause fixed drug eruption (FDE). FDE may present as a more severe variant known as generalized bullous fixed drug eruption (GBFDE), which can be life-threatening. These serious events may occur without warning. Inform patients about the signs and symptoms of serious skin reactions, and to discontinue the use of oxycodone and aspirin tablets at the first appearance of skin rash or any other sign of hypersensitivity. Oxycodone and aspirin tablets is contraindicated in patients with previous serious skin reactions to NSAIDs [see Contraindications].

Drug reaction with eosinophilia and systemic symptoms (DRESS) has been reported in patients taking NSAIDs such as oxycodone and aspirin tablets. Some of these events have been fatal or life-threatening. DRESS typically, although not exclusively, presents with fever, rash, lymphadenopathy, and/or facial swelling. Other clinical manifestations may include hepatitis, nephritis, hematological abnormalities, myocarditis, or myositis. Sometimes symptoms of DRESS may resemble an acute viral infection. Eosinophilia is often present. Because this disorder is variable in its presentation, other organ systems not noted here may be involved. It is important to note that early manifestations of hypersensitivity, such as fever or lymphadenopathy, may be present even though rash is not evident. If such signs or symptoms are present, discontinue oxycodone and aspirin tablets and evaluate the patient immediately.

Alcohol Warning

Patients who consume three or more alcoholic drinks every day should be counseled about the bleeding risks involved with chronic, heavy alcohol use while taking aspirin.

Coagulation Abnormalities

Even low doses of aspirin can inhibit platelet function leading to an increase in bleeding time. This can adversely affect patients with inherited (hemophilia) or acquired (liver disease or vitamin K deficiency) bleeding disorders.

Peptic Ulcer Disease

Patients with a history of active peptic ulcer disease should avoid using aspirin, which can cause gastric mucosal irritation and bleeding.

PRECAUTIONS

General

Aspirin has been associated with elevated hepatic enzymes, blood urea nitrogen and serum creatinine, hyperkalemia, proteinuria, and prolonged bleeding time.

Hemorrhage

Aspirin may increase the likelihood of hemorrhage due to its effect on the gastric mucosa and platelet function (prolongation of bleeding time). Salicylates should be used with caution in the presence of peptic ulcer or coagulation abnormalities.

Ambulatory Surgery and Postoperative Use

Oxycodone and other morphine-like opioids have been shown to decrease bowel motility. Ileus is a common postoperative complication, especially after intra-abdominal surgery with use of opioid analgesia. Caution should be taken to monitor for decreased bowel motility in postoperative patients receiving opioids. Standard supportive therapy should be implemented.

Information for Patients/Caregivers

Advise the patient to read the FDA-approved patient labeling (Medication Guide).

Storage and Disposal

Because of the risks associated with accidental ingestion, misuse, and abuse, advise patients to store oxycodone and aspirin tablets securely, out of sight and reach of children, and in a location not accessible by others, including visitors to the home. Inform patients that leaving oxycodone and aspirin tablets unsecured can pose a deadly risk to others in the home (see WARNINGS, DRUG ABUSE AND DEPENDENCE).

Advise patients and caregivers that when medicines are no longer needed, they should be disposed of promptly. Expired, unwanted, or unused oxycodone and aspirin tablets should be disposed of by flushing the unused medication down the toilet if a drug take-back option is not readily available. Inform patients that they can visit www.fda.gov/drugdisposal for a complete list of medicines recommended for disposal by flushing, as well as additional information on disposal of unused medicines.

Addiction, Abuse, and Misuse

Inform patients that the use of oxycodone and aspirin tablets, even when taken as recommended, can result in addiction, abuse, and misuse, which can lead to overdose and death (see WARNINGS). Instruct patients not to share oxycodone and aspirin tablets with others and to take steps to protect oxycodone and aspirin tablets from theft or misuse.

Life-Threatening Respiratory Depression

Inform patients of the risk of life-threatening respiratory depression, including information that the risk is greatest when starting oxycodone and aspirin tablets or when the dosage is increased, and that it can occur even at recommended dosages. Educate patients and caregivers on how to recognize respiratory depression and emphasize the importance of calling 911 or getting emergency medical help right away in the event of a known or suspected overdose [see WARNINGS].

Accidental Ingestion

Inform patients that accidental ingestion, especially by children, may result in respiratory depression or death (see WARNINGS).

Interactions with Benzodiazepines and Other CNS Depressants

Inform patients and caregivers that potentially fatal additive effects may occur if oxycodone and aspirin tablets is used with benzodiazepines or other CNS depressants, including alcohol, and not to use these concomitantly unless supervised by a health care provider (see WARNINGS, PRECAUTIONS; Drug Interactions).

Patient Access to Naloxone for the Emergency Treatment of Opioid Overdose

Discuss with the patient and caregiver the availability of naloxone for the emergency treatment of opioid overdose, both when initiating and renewing treatment with oxycodone and aspirin tablets. Inform patients and caregivers about the various ways to obtain naloxone as permitted by individual state naloxone dispensing and prescribing requirements or guidelines (e.g., by prescription, directly from a pharmacist, or as part of a community-based program) [see WARNINGS, DOSAGE AND ADMINISTRATION].

Educate patients and caregivers on how to recognize the signs and symptoms of an overdose.

Explain to patients and caregivers that naloxone’s effects are temporary, and that they must call 911 or get emergency medical help right away in all cases of known or suspected opioid overdose, even if naloxone is administered [see OVERDOSAGE].

If naloxone is prescribed, also advise patients and caregivers:

- How to treat with naloxone in the event of an opioid overdose
- To tell family and friends about their naloxone and to keep it in a place where family and friends can access it in an emergency
- To read the Patient Information (or other educational material) that will come with their naloxone. Emphasize the importance of doing this before an opioid emergency happens, so the patient and caregiver will know what to do.

Hyperalgesia and Allodynia

Inform patients and caregivers not to increase opioid dosage without first consulting a clinician. Advise patients to seek medical attention if they experience symptoms of hyperalgesia, including sensitivity to pain, or new pain [see WARNINGS; ADVERSE REACTIONS].

Serotonin Syndrome

Inform patients that oxycodone and aspirin tablets could cause a rare but potentially life-threatening condition called serotonin syndrome resulting from concomitant administration of serotonergic drugs. Warn patients of the symptoms of serotonin syndrome and to seek medical attention right away if symptoms develop. Instruct patients to inform their physicians if they are taking, or plan to take serotonergic medications.

MAOI Interaction

Inform patients to avoid taking oxycodone and aspirin tablets while using any drugs that inhibit monoamine oxidase. Patients should not start MAOIs while taking oxycodone and aspirin tablets (see PRECAUTIONS; Drug Interactions).

Important Administration Instructions

Instruct patients how to properly take oxycodone and aspirin tablets. The usual dosage is one tablet every 6 hours as needed for pain. The maximum daily dose of aspirin should not exceed 4 grams (see DOSAGE AND ADMINISTRATION, PRECAUTIONS)

Important Discontinuation Instructions

In order to avoid developing withdrawal symptoms, instruct patients not to discontinue oxycodone and aspirin tablets without first discussing a tapering plan with the prescriber (see DOSAGE AND ADMINISTRATION).

Driving or Operating Heavy Machinery

Inform patients that oxycodone and aspirin tablets may impair the ability to perform potentially hazardous activities such as driving a car or operating heavy machinery. Advise patients not to perform such tasks until they know how they will react to the medication [see WARNINGS].

Constipation

Advise patients of the potential for severe constipation, including management instructions and when to seek medical attention [see ADVERSE REACTIONS, CLINICAL PHARMACOLOGY].

Adrenal Insufficiency

Inform patients that oxycodone and aspirin tablets could cause adrenal insufficiency, a potentially life-threatening condition. Adrenal insufficiency may present with non-specific symptoms and signs such as nausea, vomiting, anorexia, fatigue, weakness, dizziness, and low blood pressure. Advise patients to seek medical attention if they experience a constellation of these symptoms [see WARNINGS].

Hypotension

Inform patients that oxycodone and aspirin tablets may cause orthostatic hypotension and syncope. Instruct patients how to recognize symptoms of low blood pressure and how to reduce the risk of serious consequences should hypotension occur (e.g., sit or lie down, carefully rise from a sitting or lying position).

Anaphylaxis

Inform patients that anaphylaxis have been reported with ingredients contained in oxycodone and aspirin tablets. Advise patients how to recognize such a reaction and when to seek medical attention (see CONTRAINDICATIONS, ADVERSE REACTIONS).

Pregnancy

Neonatal Opioid Withdrawal Syndrome

Inform female patients of reproductive potential that use of oxycodone and aspirin tablets for an extended period of time during pregnancy can result in neonatal opioid withdrawal syndrome, which may be life-threatening if not recognized and treated (see WARNINGS, PRECAUTIONS; Pregnancy)

Embryo-Fetal Toxicity

Inform female patients of reproductive potential that oxycodone and aspirin tablets can cause fetal harm and to inform the healthcare provider of a known or suspected pregnancy. Inform pregnant women to avoid use of aspirin and other NSAIDs starting at 30 weeks gestation because of the risk of the premature closing of the fetal ductus arteriosus. If treatment with oxycodone and aspirin tablets is needed for a pregnant woman between about 20 to 30 weeks gestation, advise her that she may need to be monitored for oligohydramnios, if treatment continues for longer than 48 hours [see WARNINGS; Fetal Toxicity, PRECAUTIONS; Pregnancy].

Lactation

Advise breastfeeding women using oxycodone and aspirin tablets to carefully observe infants for increased sleepiness (more than usual), breathing difficulties, or limpness. Instruct breastfeeding women to seek immediate medical care if they notice these signs.

Infertility

Inform patients that use of opioids for an extended period of time may cause reduced fertility. It is not known whether these effects on fertility are reversible (see ADVERSE REACTIONS).

Serious Skin Reactions, including DRESS

Advise patients to stop taking oxycodone and aspirin tablets immediately if they develop any type of rash or fever and to contact their healthcare provider as soon as possible [see WARNINGS].

Laboratory Tests

Although oxycodone may cross-react with some drug urine tests, no available studies were found which determined the duration of detectability of oxycodone in urine drug screens. However, based on pharmacokinetic data, the approximate duration of detectability for a single dose of oxycodone is roughly estimated to be one to two days following drug exposure.

Urine testing for opiates may be performed to determine illicit drug use and for medical reasons such as evaluation of patients with altered states of consciousness or monitoring efficacy of drug rehabilitation efforts. The preliminary identification of opiates in urine involves the use of an immunoassay screening and thin-layer chromatography (TLC). Gas chromatography/mass spectrometry (GC/MS) may be utilized as a third-stage identification step in the medical investigational sequence for opiate testing after immunoassay and TLC. The identities of 6-keto opiates (e.g., oxycodone) can further be differentiated by the analysis of their methoxime-trimethylsilyl (MO-TMS) derivative.

Table 1: Clinically Significant Drug Interactions with Oxycodone and Aspirin Tablets
Inhibitors of CYP3A4 and CYP2D6
Clinical Impact: | The concomitant use of oxycodone and aspirin tablets and CYP3A4 inhibitors can increase the plasma concentration of oxycodone, resulting in increased or prolonged opioid effects. These effects could be more pronounced with concomitant use of oxycodone and aspirin tablets and CYP2D6 and CYP3A4 inhibitors, particularly when an inhibitor is added after a stable dose of oxycodone and aspirin tablets is achieved (see WARNINGS). After stopping a CYP3A4 inhibitor, as the effects of the inhibitor decline, the oxycodone plasma concentration will decrease (see CLINICAL PHARMACOLOGY), resulting in decreased opioid efficacy or a withdrawal syndrome in patients who had developed physical dependence to oxycodone.
Intervention: | If concomitant use is necessary, consider dosage reduction of oxycodone and aspirin tablets until stable drug effects are achieved. Evaluate patients at frequent intervals for respiratory depression and sedation. If a CYP3A4 inhibitor is discontinued, consider increasing the oxycodone and aspirin tablets dosage until stable drug effects are achieved. Assess for signs of opioid withdrawal.
Examples | Macrolide antibiotics (e.g., erythromycin), azole-antifungal agents (e.g. ketoconazole), protease inhibitors (e.g., ritonavir)
CYP3A4 Inducers
Clinical Impact: | The concomitant use of oxycodone and aspirin tablets and CYP3A4 inducers can decrease the plasma concentration of oxycodone (see CLINICAL PHARMACOLOGY), resulting in decreased efficacy or onset of a withdrawal syndrome in patients who have developed physical dependence to oxycodone (see WARNINGS). After stopping a CYP3A4 inducer, as the effects of the inducer decline, the oxycodone plasma concentration will increase (see CLINICAL PHARMACOLOGY), which could increase or prolong both the therapeutic effects and adverse reactions, and may cause serious respiratory depression.
Intervention: | If concomitant use is necessary, consider increasing the oxycodone and aspirin tablets dosage until stable drug effects are achieved. Assess for signs of opioid withdrawal and sedation. If a CYP3A4 inducer is discontinued, consider oxycodone and aspirin tablets dosage reduction and evaluate patients at frequent intervals for signs of respiratory depression and sedation.
Examples: | Rifampin, carbamazepine, phenytoin
Benzodiazepines and other Central Nervous System (CNS) Depressants
Clinical Impact: | Due to additive pharmacologic effect, the concomitant use of benzodiazepines or other CNS depressants including alcohol, increases the risk of respiratory depression, profound sedation, coma, and death.
Intervention: | Reserve concomitant prescribing of these drugs for use in patients for whom alternative treatment options are inadequate. Limit dosages and durations to the minimum required. Inform patients and caregivers of this potential interaction and educate them on the signs and symptoms of respiratory depression (including sedation). If concomitant use is warranted, consider prescribing naloxone for the emergency treatment of opioid overdose [see WARNINGS].
Examples: | Benzodiazepines and other sedatives/hypnotics, anxiolytics, tranquilizers, muscle relaxants, general anesthetics, antipsychotics, other opioids, alcohol.
Serotonergic Drugs
Clinical Impact: | The concomitant use of opioids with other drugs that affect the serotonergic neurotransmitter system has resulted in serotonin syndrome.
Intervention: | If concomitant use is warranted, frequently evaluate the patient, particularly during treatment initiation and dose adjustment. Discontinue oxycodone and aspirin tablets if serotonin syndrome is suspected.
Examples: | Selective serotonin reuptake inhibitors (SSRIs), serotonin and norepinephrine reuptake inhibitors (SNRIs), tricyclic antidepressants (TCAs), triptans, 5-HT3 receptor antagonists, drugs that effect the serotonin neurotransmitter system (e.g., mirtazapine, trazodone, tramadol),), certain muscle relaxants (i.e., cyclobenzaprine, metaxalone), monoamine oxidase (MAO) inhibitors (those intended to treat psychiatric disorders and also others, such as linezolid and intravenous methylene blue).
Monoamine Oxidase Inhibitors (MAOIs)
Clinical Impact: | MAOI interactions with opioids may manifest as serotonin syndrome or opioid toxicity (e.g., respiratory depression, coma) (see WARNINGS).
Intervention: | The use of oxycodone and aspirin tablets is not recommended for patients taking MAOIs or within 14 days of stopping such treatment. If urgent use of an opioid is necessary, use test doses and frequent titration of small doses to treat pain while closely monitoring blood pressure and signs and symptoms of CNS and respiratory depression.
Examples | phenelzine, tranylcypromine, linezolid
Mixed Agonist/Antagonist and Partial Agonist Opioid Analgesics
Clinical Impact: | May reduce the analgesic effect of oxycodone and aspirin tablets and/or precipitate withdrawal symptoms
Intervention: | Avoid concomitant use.
Examples: | Butorphanol, nalbuphine, pentazocine, buprenorphine
Muscle Relaxants
Clinical Impact: | Oxycodone may enhance the neuromuscular blocking action of skeletal muscle relaxants and produce an increased degree of respiratory depression.
Intervention: | Monitor patients for signs of respiratory depression that may be greater than otherwise expected and decrease the dosage of oxycodone and aspirin tablets and/or the muscle relaxant as necessary. Due to the risk of respiratory depression with concomitant use of muscle relaxants and opioids, consider prescribing naloxone for the emergency treatment of opioid overdose.
Diuretics
Clinical Impact: | Opioids can reduce the efficacy of diuretics by inducing the release of antidiuretic hormone.
Intervention: | Evaluate patients for signs of diminished diuresis and/or effects on blood pressure and increase the dosage of the diuretic as needed.
Anticholinergic Drugs
Clinical Impact: | The concomitant use of anticholinergic drugs may increase risk of urinary retention and/or severe constipation, which may lead to paralytic ileus.
Intervention: | Evaluate patients for signs of urinary retention or reduced gastric motility when oxycodone and aspirin tablets is used concomitantly with anticholinergic drugs.
Analgesics
Clinical Impact: | Analgesics may reduce the analgesic effect of oxycodone or may precipitate withdrawal symptoms
Intervention: | Should be administered with caution to a patient who has received or is receiving a full opioid agonist such as oxycodone.
Examples: | Pentazocine, nalbuphine, naltrexone, and butorphanol

Drug/Drug Interactions with Aspirin

Angiotensin Converting Enzyme (ACE) Inhibitors: The hyponatremic and hypotensive effects of ACE inhibitors may be diminished by the concomitant administration of aspirin due to its indirect effect on the renin-angiotensin conversion pathway.

Acetazolamide: Concurrent use of aspirin and acetazolamide can lead to high serum concentrations of acetazolamide (and toxicity) due to competition at the renal tubule for secretion.

Anticoagulant Therapy (Heparin and Warfarin): Patients on anticoagulation therapy are at increased risk for bleeding because of drug-drug interactions and the effect on platelets. Aspirin can displace warfarin from protein binding sites, leading to prolongation of both the prothrombin time and the bleeding time. Aspirin can increase the anticoagulant activity of heparin, increasing bleeding risk.

Anticonvulsants: Salicylate can displace protein-bound phenytoin and valproic acid, leading to a decrease in the total concentration of phenytoin and an increase in serum valproic acid levels.

Beta Blockers: The hypotensive effects of beta blockers may be diminished by the concomitant administration of aspirin due to inhibition of renal prostaglandins, leading to decreased renal blood flow, and salt and fluid retention.

Diuretics: The effectiveness of diuretics in patients with underlying renal or cardiovascular disease may be diminished by the concomitant administration of aspirin due to inhibition of renal prostaglandins, leading to decreased renal blood flow and salt and fluid retention.

Methotrexate: Aspirin may enhance the serious side and toxicity of methotrexate due to displacement from its plasma protein binding sites and/or reduced renal clearance.

Nonsteroidal Anti-inflammatory Drugs (NSAIDs): The concurrent use of aspirin with other NSAIDs should be avoided because this may increase bleeding or lead to decreased renal function. Aspirin may enhance the serious side effects and toxicity of ketorolac, due to displacement from its plasma protein binding sites and/or reduced renal clearance.

Oral Hypoglycemics Agents: Aspirin may increase the serum glucose-lowering action of insulin and sulfonylureas leading to hypoglycemia.

Uricosuric Agents: Salicylates antagonize the uricosuric action of probenecid or sulfinpyrazone.

Drug/Laboratory Test Interactions

Depending on the sensitivity/specificity and the test methodology, the individual components of oxycodone and aspirin tablets may cross-react with assays used in the preliminary detection of cocaine (primary urinary metabolite, benzoylecgonine) or marijuana (cannabinoids) in human urine. A more specific alternate chemical method must be used in order to obtain a confirmed analytical result. The preferred confirmatory method is gas chromatography/mass spectrometry (GC/MS). Moreover, clinical considerations and professional judgment should be applied to any drug-of-abuse test result, particularly when preliminary positive results are used.

Salicylates may increase the protein bound iodine (PBI) result by competing for the protein binding sites on pre-albumin and possibly thyroid-binding globulins.

Carcinogenesis, Mutagenesis, Impairment of Fertility

Carcinogenesis

Long-term studies in animals to evaluate the carcinogenic potential of oxycodone and aspirin have not been conducted.

Mutagenesis

The combination of oxycodone and aspirin has not been evaluated for mutagenicity. Oxycodone alone was negative in a bacterial reverse mutation assay (Ames), an in vitro chromosome aberration assay with human lymphocytes without metabolic activation and an in vivo mouse micronucleus assay. Oxycodone was clastogenic in the human lymphocyte chromosomal assay in the presence of metabolic activation and in the mouse lymphoma assay with or without metabolic activation. Aspirin induced chromosome aberrations in cultured human fibroblasts.

Impairment of Fertility

Animal studies to evaluate the effects of oxycodone on fertility have not been conducted. Aspirin has been shown to inhibit ovulation in rats.

Pregnancy

Risk Summary

Use of opioid analgesics for extended period of time during pregnancy may cause neonatal opioid withdrawal syndrome (see WARNINGS). Available data with oxycodone and aspirin tablets are insufficient to inform a drug-associated risk for major birth defects and miscarriage. Reproduction studies in rats and rabbits demonstrated that oral administration of oxycodone was not teratogenic or embryo-fetal toxic. In several published studies, treatment of pregnant rats with oxycodone at clinically relevant doses and below, resulted in neurobehavioral effects in offspring [see Data]. Based on animal data, advise pregnant women of the potential risk to a fetus.

Use of NSAIDs, including aspirin, can cause premature closure of the fetal ductus arteriosus and fetal renal dysfunction leading to oligohydramnios and, in some cases, neonatal renal impairment. Because of these risks, limit dose and duration of oxycodone and aspirin tablets use between about 20 and 30 weeks of gestation, and avoid oxycodone and aspirin tablets use at about 30 weeks of gestation and later in pregnancy [see WARNINGS; Fetal Toxicity].

Premature Closure of Fetal Ductus Arteriosus:

Use of NSAIDs, including aspirin, at about 30 weeks gestation or later in pregnancy increases the risk of premature closure of the fetal ductus arteriosus.

Oligohydramnios/Neonatal Renal Impairment:

Use of NSAIDs at about 20 weeks gestation or later in pregnancy has been associated with cases of fetal renal dysfunction leading to oligohydramnios, and in some cases, neonatal renal impairment.

Data from observational studies regarding other potential embryofetal risks of NSAID use in women in the first or second trimesters of pregnancy are inconclusive.

Based on animal data, prostaglandins have been shown to have an important role in endometrial vascular permeability, blastocyst implantation, and decidualization. In animal studies, administration of prostaglandin synthesis inhibitors such as aspirin, resulted in increased pre- and post-implantation loss. Prostaglandins also have been shown to have an important role in fetal kidney development. In published animal studies, prostaglandin synthesis inhibitors have been reported to impair kidney development when administered at clinically relevant doses.

The estimated background risk of major birth defects and miscarriage for the indicated population(s) is unknown. All pregnancies have a background risk of birth defect, loss, or other adverse outcomes. In the U.S. general population, the estimated background risk of major birth defects and miscarriage in clinically recognized pregnancies is 2% to 4% and 15% to 20% respectively.

Clinical Considerations

Fetal/Neonatal adverse reactions:
Use of opioid analgesics for extended period of time during pregnancy for medical or nonmedical purposes can result in physical dependence in the neonate and neonatal withdrawal syndrome shortly after birth.
Neonatal opioid withdrawal syndrome presents as irritability, hyperactivity and abnormal sleep pattern, high pitched cry, tremor, vomiting, diarrhea, and failure to gain weight. The onset, duration, and severity of neonatal opioid withdrawal syndrome vary based on the specific opioid used, duration of use, timing and amount of last maternal use, and rate of elimination of the drug by the newborn. Observe newborns for symptoms of neonatal opioid withdrawal syndrome, and manage accordingly (see WARNINGS).

Premature Closure of Fetal Ductus Arteriosus:

Avoid use of NSAIDs in women at about 30 weeks gestation and later in pregnancy, because

NSAIDs, including oxycodone and aspirin tablets, can cause premature closure of the fetal

ductus arteriosus [see WARNINGS; Fetal Toxicity].

Oligohydramnios/Neonatal Renal Impairment:

If an NSAID is necessary at about 20 weeks gestation or later in pregnancy, limit the use to the

lowest effective dose and shortest duration possible. If oxycodone and aspirin tablets treatment

extends beyond 48 hours, consider monitoring with ultrasound for oligohydramnios. If

oligohydramnios occurs, discontinue oxycodone and aspirin tablets and follow up according to

clinical practice [see WARNINGS; Fetal Toxicity].

Labor and Delivery

Opioids cross the placenta and may produce respiratory depression and pyscho-physiologic effects in neonates. An opioid antagonist, such as naloxone must be available for reversal of opioid-induced respiratory depression in the neonate. Oxycodone and aspirin tablets are not recommended for use in women during and immediately prior to labor, when use of shorter acting analgesics or other analgesic techniques are more appropriate. Occasionally, opioid analgesics, including oxycodone and aspirin tablets, can prolong labor through actions which temporarily reduce the strength, duration, and frequency of uterine contractions. However, this effect is not consistent and may be offset by an increased rate of cervical dilatation, which tends to shorten labor. Monitor neonates exposed to opioid analgesics during labor for signs of excess sedation and respiratory depression.

Data

Human Data

Premature Closure of Fetal Ductus Arteriosus: Published literature reports that the use of NSAIDs at about 30 weeks of gestation and later in pregnancy may cause premature closure of the fetal ductus arteriosus.

Oligohydramnios/Neonatal Renal Impairment: Published studies and postmarketing reports describe maternal NSAID use at about 20 weeks gestation or later in pregnancy associated with fetal renal dysfunction leading to oligohydramnios, and in some cases, neonatal renal impairment. These adverse outcomes are seen, on average, after days to weeks of treatment, although oligohydramnios has been infrequently reported as soon as 48 hours after NSAID initiation. In many cases, but not all, the decrease in amniotic fluid was transient and reversible with cessation of the drug. There have been a limited number of case reports of maternal NSAID use and neonatal renal dysfunction without oligohydramnios, some of which were irreversible. Some cases of neonatal renal dysfunction required treatment with invasive procedures, such as exchange transfusion or dialysis.

Methodological limitations of these postmarketing studies and reports include lack of a control group; limited information regarding dose, duration, and timing of drug exposure; and concomitant use of other medications. These limitations preclude establishing a reliable estimate of the risk of adverse fetal and neonatal outcomes with maternal NSAID use. Because the published safety data on neonatal outcomes involved mostly preterm infants, the generalizability of certain reported risks to the full-term infant exposed to NSAIDs through maternal use is uncertain.

Animal Data

Reproduction studies in rats and rabbits demonstrated that oral administration of oxycodone was not teratogenic or embryo-fetal toxic. In published studies, offspring of pregnant rats administered oxycodone during gestation have been reported to exhibit neurobehavioral effects including altered stress responses, increased anxiety-like behavior (2 mg/kg/day IV from Gestation Day 8 to 21 and Postnatal Day 1, 3, and 5; 0.3-times an adult human dose of 60 mg/day, on a mg/m^2 basis) and altered learning and memory (15 mg/kg/day orally from breeding through parturition; 2.4 times an adult human dose of 60 mg/day, on a mg/m^2 basis).

Lactation

Risk Summary

Available data from lactation studies indicate that oxycodone is present in breastmilk and that doses of less than 60 mg/day of the immediate-release formulation are unlikely to result in clinically relevant exposures in breastfed infants. A pharmacokinetics study utilizing opportunistic sampling of 76 lactating women receiving oxycodone immediate-release products for postpartum pain management showed that oxycodone concentrates in breastmilk with an average milk to plasma ratio of 3.2. The relative infant dose was low, approximately 1.3% of a weight-adjusted maternal dose (see Data).

In the same study, among the 70 infants exposed to oxycodone in breastmilk, no adverse events were attributed to oxycodone. However, based on known adverse effects in adults, infants should be monitored for signs of excess sedation and respiratory depression (see Clinical Considerations). There are no data on the effects of the oxycodone on milk production.

Salicylic acid has been detected in breast milk. Adverse effects on platelet function in the nursing infant exposed to aspiring in breast milk may be a potential risk. Furthermore, the risk of Reye Syndrome cause by salicylate in breast milk is unknown. The developmental and health benefits of breastfeeding should be considered along with the mother’s clinical need for oxycodone and aspirin tablets and any potential adverse effects on the breastfed child from oxycodone and aspirin tablets or from the underlying maternal condition.

Clinical Considerations

Monitor infants exposed to oxycodone and aspirin tablets through breast milk for excess sedation and respiratory depression. Withdrawal symptoms can occur in breastfed infants when maternal administration of an opioid analgesic is stopped or when breastfeeding is stopped.

Data

Oxycodone concentration data from 76 lactating women receiving immediate-release oxycodone products for postpartum pain management, and 28 infants exposed to oxycodone in breastmilk showed that following a median (range) dose of oxycodone in mothers of 9.2 (5-10) mg/dose or 33.0 (5.4-59.3) mg/day, oxycodone concentrated in breastmilk with a median (range) milk to plasma ratio of 3.2 (1.2-5.3). However, when using maternal breastmilk data to estimate the daily and relative infant dose, the infant dose was 0.006 mg/kg/day, which is 1.3% of a weight-adjusted maternal dose of 10 mg every 6 hours. These estimates based on maternal breastmilk concentrations were corroborated by the observed infant concentrations, of which over 75% (19/25) were below the limit of quantification. Among the 6 infants with quantifiable concentration, the median (range) concentration was 0.2 ng/mL (0.1-0.7). These concentrations are 100 to 1000 times lower than concentrations observed in other studies after infants received oxycodone at 0.1 mg/kg/dose (~20- 200 ng/mL).

Females and Males of Reproductive Potential

Infertility

Use of opioids for an extended period of time may cause reduced fertility in females and males of reproductive potential. It is not known whether these effects on fertility are reversible.

Pediatric Use

Oxycodone and aspirin tablets should not be administered to pediatric patients. Reye Syndrome is a rare but serious disease which can follow flu or chicken pox in children and teenagers. While the cause of Reye Syndrome is unknown, some reports claim aspirin (or salicylates) may increase the risk of developing this disease.

Geriatric Use

Elderly patients (aged 65 years or older) may have increased sensitivity to oxycodone. In general, use caution when selecting a dosage for an elderly patient, usually starting at the low end of the dosing range, reflecting the greater frequency of decreased hepatic, renal, or cardiac function and of concomitant disease or other drug therapy.

Respiratory depression is the chief risk for elderly patients treated with opioids, and has occurred after large initial doses were administered to patients who were not opioid-tolerant or when opioids were co-administered with other agents that depress respiration. Titrate the dosage of oxycodone and aspirin tablets slowly in geriatric patients and frequently reevaluate the patients for signs of central nervous system and respiratory depression.

This drug is known to be substantially excreted by the kidney, and the risk of adverse reactions to this drug may be greater in patients with impaired renal function. Because elderly patients are more likely to have decreased renal function, care should be taken in dose selection, and it may be useful to regularly evaluate renal function.

Hepatic Impairment

In a pharmacokinetic study of oxycodone in patients with end-stage liver disease, oxycodone plasma clearance decreased and the elimination half-life increased. Care should be exercised when oxycodone is used in patients with hepatic impairment.

Avoid aspirin in patients with severe hepatic impairment.

Renal Impairment

In a study of patients with end stage renal impairment, mean elimination half-life of oxycodone was prolonged in uremic patients due to increased volume of distribution and reduced clearance. Oxycodone should be used with caution in patients with renal impairment.

Avoid aspirin in patients with severe renal impairment (glomerular filtration rate less than 10 mL/minute).

ADVERSE REACTIONS

The following serious adverse reactions are described, or described in greater detail, in other sections:

- Addiction, Abuse, and Misuse (see WARNINGS)
- Life-Threatening Respiratory Depression (see WARNINGS)
- Neonatal Opioid Withdrawal Syndrome (see WARNINGS)
- Opioid-Induced Hyperalgesia and Allodynia [see WARNINGS]
- Interactions with Benzodiazepines and Other CNS Depressants (see WARNINGS)
- Adrenal Insufficiency (see WARNINGS)
- Severe Hypotension (see WARNINGS)
- Gastrointestinal Adverse Reactions (see WARNINGS)
- Seizures (see WARNINGS)
- Withdrawal (see WARNINGS)

Clinical Trials Experience

Because clinical trials are conducted under widely varying conditions, adverse reaction rates observed in the clinical trials of a drug cannot be directly compared to rates in the clinical trials of another drug and may not reflect the rates observed in practice.

Serious adverse reactions that may be associated with oxycodone and aspirin tablet use include, apnea, circulatory depression, hypotension, respiratory arrest, respiratory depression, and shock (see OVERDOSAGE).

The most frequently observed non-serious adverse reactions include lightheadedness, dizziness, drowsiness or sedation, nausea, and vomiting. These effects seem to be more prominent in ambulatory than in nonambulatory patients, and some of these adverse reactions may be alleviated if the patient lies down. Other adverse reactions include euphoria, dysphoria, constipation and pruritus.

Aspirin may increase the likelihood of hemorrhage due to its effect on the gastric mucosa and platelet function. Furthermore, aspirin has the potential to cause anaphylaxis in hypersensitive patients as well as angioedema especially in patients with chronic urticaria. Other adverse reactions due to aspirin use include anorexia, reversible hepatotoxicity, leukopenia, thrombocytopenia, purpura, decreased plasma iron concentration, and shortened erythrocyte survival time.

Postmarketing Experience

The following adverse reactions have been identified during post approval use of oxycodone. Because these reactions are reported voluntarily from a population of uncertain size, it is not always possible to reliably estimate their frequency or establish a causal relationship to drug exposure.

The adverse reactions obtained from postmarketing experiences with oxycodone and aspirin tablets are listed by organ system and in decreasing order of severity and/or frequency as follows:

Body as a Whole

allergic reaction, malaise, asthenia, headache, anaphylaxis, fever, hypothermia, thirst, increased sweating, accident, accidental overdose, non-accidental overdose.

Cardiovascular

tachycardia, dysrhythmias, hypotension, orthostatic hypotension, bradycardia, palpitations

Central and Peripheral Nervous System

stupor, paresthesia, agitation, cerebral edema, coma, confusion, dizziness, headache, subdural or intracranial hemorrhage, lethargy, seizures, anxiety, mental impairment

Fluid and Electrolyte

dehydration, hyperkalemia, metabolic acidosis, respiratory alkalosis

Gastrointestinal

hemorrhagic gastric/duodenal ulcer, gastric/peptic ulcer, dyspepsia, abdominal pain, diarrhea, eructation, dry mouth, gastrointestinal bleeding, intestinal perforation, nausea, vomiting, transient elevations of hepatic enzymes, hepatitis, Reye syndrome, pancreatitis, intestinal obstruction, ileus

Hearing and Vestibular

hearing loss, tinnitus. Patients with high frequency loss may have difficulty perceiving tinnitus. In these patients, tinnitus cannot be used as a clinical indicator of salicylism.

Hematologic

unspecified hemorrhage, purpura, reticulocytosis, prolongation of prothrombin time, disseminated intravascular coagulation, ecchymosis, thrombocytopenia

Hypersensitivity

acute anaphylaxis, angioedema, asthma, bronchospasm, laryngeal edema, urticaria, anaphylactoid reaction

Metabolic and Nutritional

hypoglycemia, hyperglycemia, acidosis, alkalosis

Musculoskeletal rhabdomyolysis

Ocular

miosis, visual disturbances, red eye

Psychiatric

drug dependence, drug abuse, somnolence, depression, nervousness, hallucination

Reproductive

prolonged pregnancy and labor, stillbirths, lower birth weight infants, antepartum and postpartum bleeding, closure of patent ductus arteriosis

Respiratory System

bronchospasm, dyspnea, hyperpnea, pulmonary edema, tachypnea, aspiration, hypoventilation, laryngeal edema

Skin and Appendages

urticaria, rash, flushing, exfoliative dermatitis, Stevens-Johnson Syndrome (SJS), toxic epidermal necrolysis (TEN), and fixed drug eruption (FDE).

Urogenital

interstitial nephritis, papillary necrosis, proteinuria, renal insufficiency and failure, urinary retention

Serotonin syndrome

Cases of serotonin syndrome, a potentially life-threatening condition, have been reported during concomitant use of opioids with serotonergic drugs.

Adrenal insufficiency

Cases of adrenal insufficiency have been reported with opioid use, more often following greater than one month of use.

Anaphylaxis

Anaphylaxis has been reported with ingredients contained in oxycodone and aspirin tablets.

Androgen deficiency

Cases of androgen deficiency have occurred with the use of opioids for an extended period of time (see CLINICAL PHARMACOLOGY).

Hyperalgesia and Allodynia: Cases of hyperalgesia and allodynia have been reported with opioid therapy of any duration [see WARNINGS]

Hypoglycemia: Cases of hypoglycemia have been reported in patients taking opioids. Most reports were in patients with at least one predisposing risk factor (e.g., diabetes).

OVERDOSAGE

Clinical Presentation

Acute overdose with oxycodone can be manifested by respiratory depression, somnolence progressing to stupor or coma, skeletal muscle flaccidity, cold and clammy skin, constricted pupils, and, in some cases, pulmonary edema, bradycardia, hypotension, hypoglycemia, partial or complete airway obstruction, atypical snoring, and death. Marked mydriasis rather than miosis may be seen with hypoxia in overdose situations [see CLINICAL PHARMACOLOGY].

Early signs of acute aspirin (salicylate) overdose including tinnitus occur at plasma concentrations approaching 200 mcg/mL. Plasma concentrations of aspirin above 300 mcg/mL are toxic. Severe toxic effects are associated with levels above 400 mcg/mL. A single lethal dose of aspirin in adults is not known with certainty but death may be expected at 30 g. For real or suspected overdose, a Poison Control Center should be contacted immediately.

In acute salicylate overdose, severe acid-base and electrolyte disturbances may occur and are complicated by hyperthermia and dehydration, and coma. Respiratory alkalosis occurs early while hyperventilation is present, but is quickly followed by metabolic acidosis. Serious symptoms such as depression, coma, and respiratory failure progress rapidly.

Salicylism (chronic salicylate toxicity) may be noted by symptoms such as dizziness, tinnitus, difficulty hearing, nausea, vomiting, diarrhea, and mental confusion. More severe salicylism may result in respiratory alkalosis.

Treatment of Overdose

In case of overdose, priorities are the reestablishment of a patent and protected airway and institution of assisted or controlled ventilation, if needed. Employ other supportive measures (including oxygen and vasopressors) in the management of circulatory shock and pulmonary edema as indicated. Cardiac arrest or arrhythmias will require advanced life-support measures.

Opioid antagonists, such as naloxone, are specific antidotes to respiratory depression resulting from opioid overdose. For clinically significant respiratory or circulatory depression secondary to opioid overdose, administer an opioid antagonist.

Because the duration of opioid reversal is expected to be less than the duration of action of oxycodone in oxycodone and aspirin tablets, carefully monitor the patient until spontaneous respiration is reliably re-established. If the response to an opioid antagonist is suboptimal or only brief in nature, administer additional antagonist as directed by the product’s prescribing information.

In an individual physically dependent on opioids, administration of the recommended usual dosage of the antagonist will precipitate an acute withdrawal syndrome. The severity of the withdrawal symptoms experienced will depend on the degree of physical dependence and the dose of the antagonist administered. If a decision is made to treat serious respiratory depression in the physically dependent patient, administration of the antagonist should be begun with care and by titration with smaller than usual doses of the antagonist.

DOSAGE AND ADMINISTRATION

Important Dosage and Administration Instructions

Oxycodone and aspirin tablets should be prescribed only by healthcare professionals who are knowledgeable about the use of opioids and how to mitigate the associated risks.

Use the lowest effective dosage for the shortest duration of time consistent with individual patient treatment goals [see WARNINGS]. Because the risk of overdose increases as opioid doses increase, reserve titration to higher doses of oxycodone and aspirin tablets for patients in whom lower doses are insufficiently effective and in whom the expected benefits of using a higher dose opioid clearly outweigh the substantial risks.

Many acute pain conditions (e.g., the pain that occurs with a number of surgical procedures or acute musculoskeletal injuries) require no more than a few days of an opioid analgesic. Clinical guidelines on opioid prescribing for some acute pain conditions are available.

There is variability in the opioid analgesic dose and duration needed to adequately manage pain due both to the cause of pain and to individual patient factors. Initiate the dosing regimen for each patient individually, taking into account the patient’s underlying cause and severity of pain, prior analgesic treatment and response, and risk factors for addiction, abuse, and misuse [see WARNINGS].

Respiratory depression can occur at any time during opioid therapy, especially when initiating and following dosage increases with oxycodone and aspirin tablets. Consider this risk when selecting an initial dose and when making dose adjustments [see WARNINGS].

Patient Access to Naloxone for the Emergency Treatment of Opioid Overdose

Discuss the availability of naloxone for the emergency treatment of opioid overdose with the patient and caregiver and assess the potential need for access to naloxone, both when initiating and renewing treatment with oxycodone and aspirin tablets [see WARNINGS, PRECAUTIONS; Information for Patients/Caregivers].

Inform patients and caregivers about the various ways to obtain naloxone as permitted by individual state naloxone dispensing and prescribing regulations (e.g., by prescription, directly from a pharmacist, or as part of a community-based program).

Consider prescribing naloxone, based on the patient’s risk factors for overdose, such as concomitant use of CNS depressants, a history of opioid use disorder, or prior opioid overdose. The presence of risk factors for overdose should not prevent the proper management of pain in any given patient [see WARNINGS; Addiction, Abuse, and Misuse; Life-Threatening Respiratory Depression; Risks from Concomitant Use with Benzodiazepines or Other CNS Depressants].

Consider prescribing naloxone when the patient has household members (including children) or other close contacts at risk for accidental ingestion or overdose.

Initial Dosage

Initiating Treatment with Oxycodone and Aspirin Tablets

Initiate treatment with one tablet every 6 hours as needed for pain, and at lowest dose necessary to achieve adequate analgesia. Titrate the dose based upon the individual patient’s response to their initial dose of oxycodone and aspirin tablets. The maximum daily dose of aspirin should not exceed 4 grams or 12 tablets.

Titration and Maintenance of Therapy

Individually titrate oxycodone and aspirin tablets to a dose that provides adequate analgesia and minimizes adverse reactions. Continually reevaluate patients receiving oxycodone and aspirin tablets to assess the maintenance of pain control, signs and symptoms of opioid withdrawal, and other adverse reactions, as well to reassess for the development of addiction, abuse, or misuse (see WARNINGS). Frequent communication is important among the prescriber, other members of the healthcare team, the patient, and the caregiver/family during periods of changing analgesic requirements, including initial titration.

If the level of pain increases after dosage stabilization, attempt to identify the source of increased pain before increasing the oxycodone and aspirin tablets dosage. If after increasing the dosage, unacceptable opioid-related adverse reactions are observed (including an increase in pain after a dosage increase), consider reducing the dosage [see WARNINGS]. Adjust the dosage to obtain an appropriate balance between management of pain and opioid-related adverse reactions.

Safe Reduction or Discontinuation of Oxycodone and Aspirin Tablets

Do not abruptly discontinue oxycodone and aspirin tablets in patients who may be physically dependent on opioids. Rapid discontinuation of opioid analgesics in patients who are physically dependent on opioids has resulted in serious withdrawal symptoms, uncontrolled pain, and suicide. Rapid discontinuation has also been associated with attempts to find other sources of opioid analgesics, which may be confused with drug-seeking for abuse. Patients may also attempt to treat their pain or withdrawal symptoms with illicit opioids, such as heroin, and other substances.

When a decision has been made to decrease the dose or discontinue therapy in an opioid-dependent patient taking oxycodone and aspirin tablets, there are a variety of factors that should be considered, including the total daily dose of opioid (including oxycodone and aspirin tablets) the patient has been taking, the duration of treatment, the type of pain being treated, and the physical and psychological attributes of the patient. It is important to ensure ongoing care of the patient and to agree on an appropriate tapering schedule and follow-up plan so that patient and provider goals and expectations are clear and realistic. When opioid analgesics are being discontinued due to a suspected substance use disorder, evaluate and treat the patient, or refer for evaluation and treatment of the substance use disorder. Treatment should include evidence-based approaches, such as medication assisted treatment of opioid use disorder. Complex patients with comorbid pain and substance use disorders may benefit from referral to a specialist.

There are no standard opioid tapering schedules that are suitable for all patients. Good clinical practice dictates a patient-specific plan to taper the dose of the opioid gradually. For patients on oxycodone and aspirin tablets who are physically opioid-dependent, initiate the taper by a small enough increment (e.g., no greater than 10% to 25% of the total daily dose) to avoid withdrawal symptoms, and proceed with dose lowering at an interval of every 2 to 4 weeks. Patients who have been taking opioids for briefer periods of time may tolerate a more rapid taper.

It may be necessary to provide the patient with lower dosage strengths to accomplish a successful taper. Reassess the patient frequently to manage pain and withdrawal symptoms, should they emerge. Common withdrawal symptoms include restlessness, lacrimation, rhinorrhea, yawning, perspiration, chills, myalgia, and mydriasis. Other signs and symptoms also may develop, including irritability, anxiety, backache, joint pain, weakness, abdominal cramps, insomnia, nausea, anorexia, vomiting, diarrhea, or increased blood pressure, respiratory rate, or heart rate. If withdrawal symptoms arise, it may be necessary to pause the taper for a period of time or raise the dose of the opioid analgesic to the previous dose, and then proceed with a slower taper. In addition, evaluate patients for any changes in mood, emergence of suicidal thoughts, or use of other substances.

When managing patients taking opioid analgesics, particularly those who have been treated for an extended period of time and/or with high doses for chronic pain, ensure that a multimodal approach to pain management, including mental health support (if needed), is in place prior to initiating an opioid analgesic taper. A multimodal approach to pain management may optimize the treatment of chronic pain, as well as assist with the successful tapering of the opioid analgesic (see WARNINGS; Withdrawal, DRUG ABUSE AND DEPENDENCE).

DRUG ABUSE AND DEPENDENCE

Controlled Substance

Oxycodone and aspirin tablets contain oxycodone, a Schedule II controlled substance.

Abuse

Oxycodone and aspirin tablets contains oxycodone, a substance with high potential for misuse and abuse, which can lead to the development of substance use disorder, including addiction [see WARNINGS].

Misuse is the intentional use, for therapeutic purposes, of a drug by an individual in a way other than prescribed by a healthcare provider or for whom it was not prescribed.

Abuse is the intentional, non-therapeutic use of a drug, even once, for its desirable psychological or physiological effects.

Drug addiction is a cluster of behavioral, cognitive, and physiological phenomena that may include a strong desire to take the drug, difficulties in controlling drug use (e.g., continuing drug use despite harmful consequences, giving a higher priority to drug use than other activities and obligations), and possible tolerance or physical dependence.

Misuse and abuse of oxycodone and aspirin tablets increases risk of overdose, which may lead to central nervous system and respiratory depression, hypotension, seizures, and death. The risk is increased with concurrent abuse of oxycodone and aspirin tablets with alcohol and/or other CNS depressants. Abuse of and addiction to opioids in some individuals may not be accompanied by concurrent tolerance and symptoms of physical dependence. In addition, abuse of opioids can occur in the absence of addiction.

All patients treated with opioids require careful and frequent reevaluation for signs of misuse, abuse, and addiction, because use of opioid analgesic products carries the risk of addiction even under appropriate medical use. Patients at high risk of oxycodone and aspirin tablets abuse include those with a history of prolonged use of any opioid, including products containing oxycodone, those with a history of drug or alcohol abuse, or those who use oxycodone and aspirin tablets in combination with other abused drugs.

“Drug-seeking” behavior is very common in persons with substance use disorders. Drug-seeking tactics include emergency calls or visits near the end of office hours, refusal to undergo appropriate examination, testing, or referral, repeated “loss” of prescriptions, tampering with prescriptions, and reluctance to provide prior medical records or contact information for other treating healthcare provider(s). “Doctor shopping” (visiting multiple prescribers to obtain additional prescriptions) is common among people who abuse drugs and people with substance use disorder. Preoccupation with achieving adequate pain relief can be appropriate behavior in a patient with inadequate pain control.

Oxycodone and aspirin tablets, like other opioids, can be diverted for nonmedical use into illicit channels of distribution. Careful record-keeping of prescribing information, including quantity, frequency, and renewal requests, as required by state and federal law, is strongly advised.

Proper assessment of the patient, proper prescribing practices, periodic reevaluation of therapy, and proper dispensing and storage are appropriate measures that help to limit abuse of opioid drugs.

Risks Specific to Abuse of Oxycodone and Aspirin Tablets

Oxycodone and aspirin tablets are for oral use only. Abuse of oxycodone and aspirin tablets poses a risk of overdose and death. The risk is increased with concurrent use oxycodone and aspirin tablets with alcohol and/or other CNS depressants.

Parenteral drug abuse is commonly associated with transmission of infectious diseases such as hepatitis and HIV.

Dependence

Both tolerance and physical dependence can develop during use of opioid therapy.

Tolerance is a physiological state characterized by a reduced response to a drug after repeated administration (i.e., a higher dose of a drug is required to produce the same effect that was once obtained at a lower dose).

Physical dependence is a state that develops as a result of a physiological adaptation in response to repeated drug use, manifested by withdrawal signs and symptoms after abrupt discontinuation or a significant dose reduction of a drug.

Withdrawal may be precipitated through the administration of drugs with opioid antagonist activity (e.g., naloxone), mixed agonist/antagonist analgesics (e.g., pentazocine, butorphanol, nalbuphine), or partial agonists (e.g., buprenorphine). Physical dependence may not occur to a clinically significant degree until after several days to weeks of continued use.

Do not abruptly discontinue oxycodone and aspirin tablets in a patient physically dependent on opioids. Rapid tapering of oxycodone and aspirin tablets in a patient physically dependent on opioids may lead to serious withdrawal symptoms, uncontrolled pain, and suicide. Rapid discontinuation has also been associated with attempts to find other sources of opioid analgesics, which may be confused with drug-seeking for abuse.

When discontinuing oxycodone and aspirin tablets, gradually taper the dosage using a patient specific plan that considers the following: the dose of oxycodone and aspirin tablets the patient has been taking, the duration of treatment, and the physical and psychological attributes of the patient. To improve the likelihood of a successful taper and minimize withdrawal symptoms, it is important that the opioid tapering schedule is agreed upon by the patient. In patients taking opioids for an extended period of time at high doses, ensure that a multimodal approach to pain management, including mental health support (if needed), is in place prior to initiating an opioid analgesic taper (see DOSAGE AND ADMINISTRATION, WARNINGS).

Infants born to mothers physically dependent on opioids will also be physically dependent and may exhibit respiratory difficulties and withdrawal signs.

HOW SUPPLIED

Oxycodone and Aspirin Tablets, USP are supplied as white to off-white round biconvex tablets debossed “Є” above bisect and “61” below bisect on one side, plain on the other side. They are available as follows:

NDC 42806-061-01 Bottles of 100

Store at 20°- 25°C (68° - 77°F); Dispense in a tight, light-resistant container as defined in the USP, with a child-resistant closure (as required).

DEA Order Form Required.

Store Oxycodone and Aspirin Tablets, USP securely and dispose of properly (see PRECAUTIONS; Information for Patients).

Distributed by:

Epic Pharma, LLC

Laurelton, NY 11413

Rev. 05-2025-00

MF061REV05/25

OE1245

Medication Guide

Oxycodone and Aspirin Tablets, USP

(ox-ee-CO-dohn and As-pir-in) for oral use, CII

Rx Only

Oxycodone and Aspirin Tablets is:

- A strong prescription pain medicine that contains an opioid (narcotic) that is used to manage pain severe enough to require an opioid pain medicine when other pain treatments such as non-opioid pain medicines do not treat your pain well enough or you cannot tolerate them.
- An opioid pain medicine that can put you at risk for overdose and death. Even if you take your dose correctly as prescribed you are at risk for opioid addiction, abuse, and misuse that can lead to death.

Important information about Oxycodone and Aspirin Tablets :

- Get emergency help or call 911 right away if you take too much oxycodone and aspirin tablets (overdose). When you first start taking oxycodone and aspirin tablets, when your dose is changed, or if you take too much (overdose), serious or life-threatening breathing problems that can lead to death may occur. Talk to your healthcare provider about naloxone, a medicine for the emergency treatment of an opioid overdose.
- Taking oxycodone and aspirin tablets with other opioid medicines, benzodiazepines, alcohol, or other central nervous system depressants (including street drugs) can cause severe drowsiness, decreased awareness, breathing problems, coma, and death.
- Never give anyone else your oxycodone and aspirin tablets. They could die from taking it. Selling or giving away oxycodone and aspirin tablets is against the law.
- Store oxycodone and aspirin tablets securely, out of sight and reach of children, and in a location not accessible by others, including visitors to the home.

Do not take Oxycodone and Aspirin Tablets if you have:

• severe asthma, trouble breathing, or other lung problems.
• a bowel blockage or have narrowing of the stomach or intestines.

Before taking oxycodone and aspirin tablets, tell your healthcare provider if you have a history of:

- head injury, seizures

- liver, kidney, thyroid problems

- problems urinating

- pancreas or gallbladder problems

- abuse of street or prescription drugs, alcohol opioid overdose, or mental health problems.

Tell your healthcare provider if you are:

- notice your pain getting worse. If your pain gets worse after you take oxycodone and aspirin tablets, do not take more of oxycodone and aspirin tablets without first talking to your healthcare provider. Talk to your healthcare provider if the pain you have increases, if you feel more sensitive to pain, or if you have new pain after taking oxycodone and aspirin tablets.
- Are pregnant or planning to become pregnant. Use of oxycodone and aspirin tablets for an extended period of time during pregnancy can cause withdrawal symptoms in your newborn baby that could be life-threatening if not recognized and treated. Taking NSAID-containing products like oxycodone and aspirin tablets at about 20 weeks of pregnancy or later may harm your unborn baby. If you need to take NSAIDs for more than 2 days when you are between 20 and 30 weeks of pregnancy, your healthcare provider may need to monitor the amount of fluid in your womb around your baby. You should not take NSAIDs after about 30 weeks of pregnancy.
- are breastfeeding. oxycodone and aspirin tablets passes into breast milk and may harm your baby. Carefully observe infants for increased sleepiness (more than usual), breathing difficulties, or limpness. Seek immediate medical care if you notice these signs.
- develop any type of rash or fever. Contact your healthcare provider as soon as possible and stop taking oxycodone and aspirin tablets.
- are living in a household where there are small children or someone who has abused street or prescription drugs.
- are taking prescription or over-the-counter medicines, vitamins, or herbal supplements. Taking oxycodone and aspirin tablets with certain other medicines can cause serious side effects that could lead to death.

When taking Oxycodone and Aspirin Tablets:

- Do not change your dose. Take oxycodone and aspirin tablets exactly as prescribed by your healthcare provider. Use the lowest dose possible for the shortest time needed. Take your prescribed dose at the same time every day. Do not take more than your prescribed dose. If you miss a dose, take your next dose at your usual time.
- For acute (short-term) pain, you may only need to take oxycodone and aspirin tablets for a few days. You may have some oxycodone and aspirin tablets left over that you did not use. See disposal information at the bottom of this section for directions on how to safely throw away (dispose of) your unused oxycodone and aspirin tablets.
- Take your prescribed dose [one tablet every six hours] as needed for pain. Do not take more than your prescribed dose. If you miss a dose, take your next dose at your usual time.
- Call your healthcare provider if the dose you are taking does not control your pain.
- If you have been taking oxycodone and aspirin tablets regularly, do not stop taking oxycodone and aspirin tablets without talking to your healthcare provider.
- Dispose of expired, unwanted, or unused oxycodone and aspirin tablets by promptly flushing down the toilet, if a drug take-back option is not readily available. Visit www.fda.gov/drugdisposal for additional information on disposal of unused medicines.

While taking Oxycodone and Aspirin Tablets DO NOT:

- Drive or operate heavy machinery, until you know how oxycodone and aspirin tablets affects you. Oxycodone and aspirin tablets can make you sleepy, dizzy, or lightheaded.
- Drink alcohol or use prescription or over-the-counter medicines that contain alcohol. Using products containing alcohol during treatment with oxycodone and aspirin tablets may cause you to overdose and die.

The possible side effects of Oxycodone and Aspirin Tablets:

- constipation, nausea, sleepiness, vomiting, tiredness, headache, dizziness, abdominal pain, rash, or fever. Call your healthcare provider if you have any of these symptoms and they are severe.

Get emergency medical help or call 911 right away if you have:

- trouble breathing, shortness of breath, fast heartbeat, chest pain, swelling of your face, tongue or throat, extreme drowsiness, light-headedness when changing positions, feeling faint, agitation, high body temperature, trouble walking, stiff muscles, or mental changes such as confusion.

These are not all the possible side effects of oxycodone and aspirin tablets. Call your healthcare provider for medical advice about side effects. You may report side effects to FDA at 1-800-FDA-1088. For more information go to dailymed.nlm.nih.gov

This Medication Guide has been approved by the U.S. Food and Drug Administration.

For additional copies of the printed patient information/ medication guide, please visit www.epic-pharma.com or call 1-888-374-2791.

Distributed by:

Epic Pharma, LLC

Laurelton, NY 11413

Rev. 05-2025-00

OE2935

PACKAGE/LABEL PRINCIPAL DISPLAY PANEL

Oxycodone Hydrochloride, USP Cll

4.8355 mg*/325 mg

Rx Only

100 Tablets